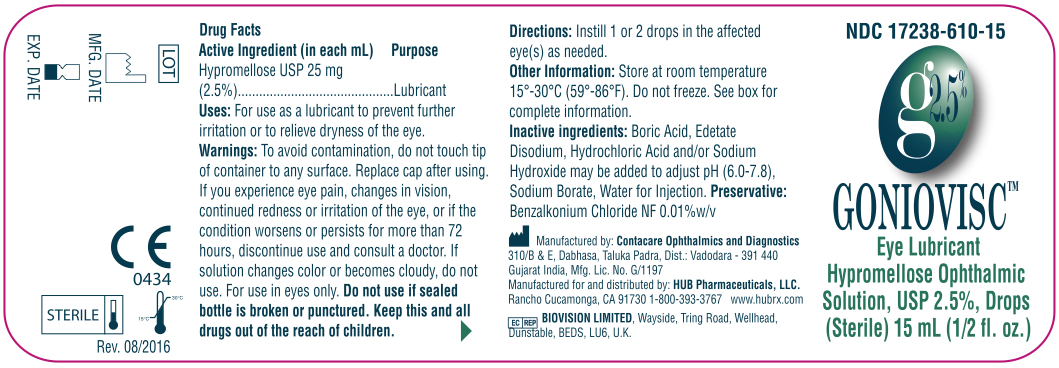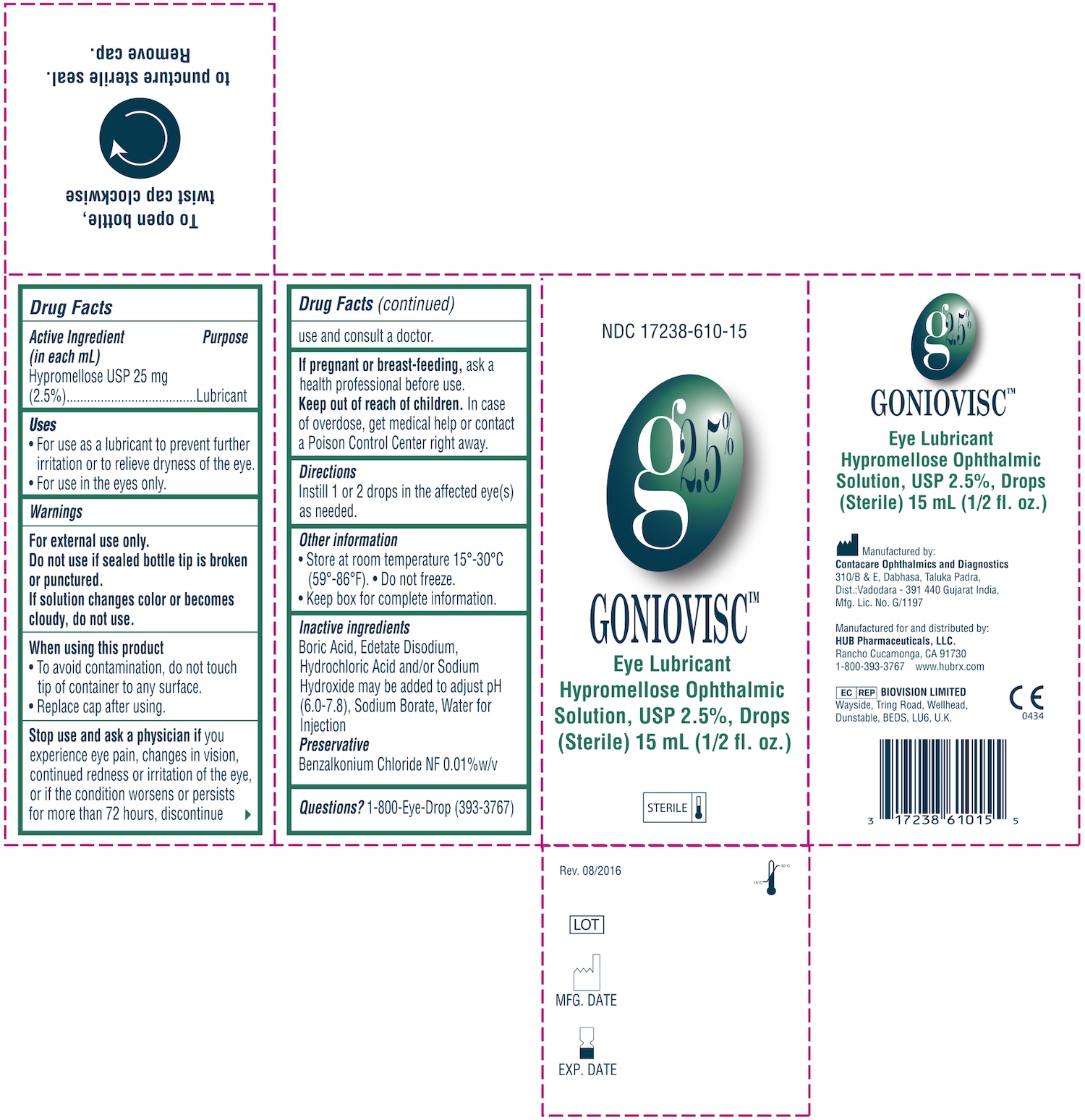 DRUG LABEL: Goniovisc
NDC: 17238-610 | Form: SOLUTION/ DROPS
Manufacturer: HUB Pharmaceuticals, LLC
Category: otc | Type: HUMAN OTC DRUG LABEL
Date: 20171226

ACTIVE INGREDIENTS: HYPROMELLOSE 2910 (4000 MPA.S) 25 mg/1 mL
INACTIVE INGREDIENTS: BORIC ACID; EDETATE DISODIUM; SODIUM BORATE; WATER; HYDROCHLORIC ACID; SODIUM HYDROXIDE; BENZALKONIUM CHLORIDE

GONIOVISC Eye Lubricant Hypromellose Ophthalmic Solution, USP 2.5%, Drops (Sterile)

ACTIVE INGREDIENTS:

Active Ingredients Purpose

Hypromellose 25 mg (2.5%)......Lubricant

USES:

- For use as a lubricant to prevent further irritation or to relieve dryness of the eye.
- For use in the eyes only.

Indications & Usage:

For use as a lubricant to prevent further irritation or to relieve dryness of the eye.

WARNINGS:

- For external use only.
- Do not use if sealed bottle tip is broken or punctured.
- If solution changes color or becomes cloudy, do not use.

When using this product

- To avoid contamination, do not touch tip of container to any surface.
- Replace cap after using.

Stop use and ask a physician

If you experience eye pain, changes in vision, continued redness or irritation of the eye, or if the condition worsens or persists for more than 72 hours, discontinue use and consult a doctor.

If pregnant or breast-feeding,

ask a health professional before use.

Keep out of reach of children.

In case of overdose, get medical help or contact a Poison Control Center right away.

DIRECTIONS:

Instill 1 or 2 drops in the affected eye(s) as needed.

OTHER INFORMATION:

- Store at room temperature 15°-30°C (59°-86°F).
- Do not freeze.
- Keep box for complete information.

INACTIVE INGREDIENTS:

- Boric Acid
- Edetate Disodium
- Hydrochloric Acid and/or Sodium Hydroxide may be added to adjust pH (6.0-7.8)
- Sodium Borate
- Water for Injection

Preservative:

- Benzalkonium Chloride Solution NF 0.02% v/v

Questions?

1-800-Eye-Drop (393-3767)

PACKAGE LABELS:

Image 1: Label for Bottle

Image 2: Label for Box